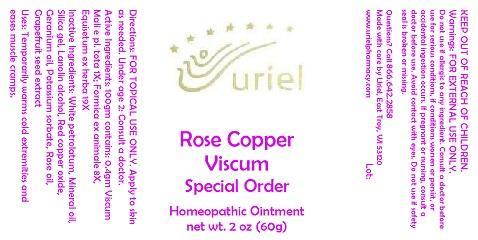 DRUG LABEL: Rose Copper Viscum Special Order
NDC: 48951-8297 | Form: OINTMENT
Manufacturer: Uriel Pharmacy Inc.
Category: homeopathic | Type: HUMAN OTC DRUG LABEL
Date: 20140912

ACTIVE INGREDIENTS: VISCUM ALBUM FRUITING TOP 1 [hp_X]/1 g; FORMICA RUFA 8 [hp_X]/1 g; EQUISETUM ARVENSE TOP 19 [hp_X]/1 g
INACTIVE INGREDIENTS: PETROLATUM; MINERAL OIL; COLLOIDAL SILICON DIOXIDE; LANOLIN ALCOHOLS; CUPROUS OXIDE; GERANIUM OIL, ALGERIAN TYPE; POTASSIUM SORBATE; ROSE OIL; CITRUS PARADISI SEED

Rose Copper Viscum Special Order

INDICATIONS AND USAGE

Directions: FOR TOPICAL USE ONLY.

DOSAGE AND ADMINISTRATION

Apply to skin as needed. Under age 2: Consult a doctor.

ACTIVE INGREDIENT

Active Ingredients: 100gm contains: 0.4gm Viscum Mali e pl. tota 1X; Formica ex animale 8X, Equisetum ex herba 19X

INACTIVE INGREDIENT

Inactive Ingredients: White petrolatum, Mineral oil, Silica gel, Lanolin alcohol, Red copper oxide, Geranium oil, Potassium sorbate, Rose oil, Grapefruit seed extract

PURPOSE

Uses: Temporarily warms cold extremities and eases muscle cramps.

KEEP OUT OF REACH OF CHILDREN.

WARNINGS

Warnings: FOR EXTERNAL USE ONLY. Do not use if allergic to any ingredient. Consult a doctor before use for serious conditions, if conditions worsen or persist, or accidental ingestion occurs. If pregnant or nursing, consult a doctor before use. Avoid contact with eyes. Do not use if safety seal is broken or missing.

QUESTIONS

Questions? Call 866.642.2858 Made with care by Uriel, East Troy, WI 53120 www.urielpharmacy.com